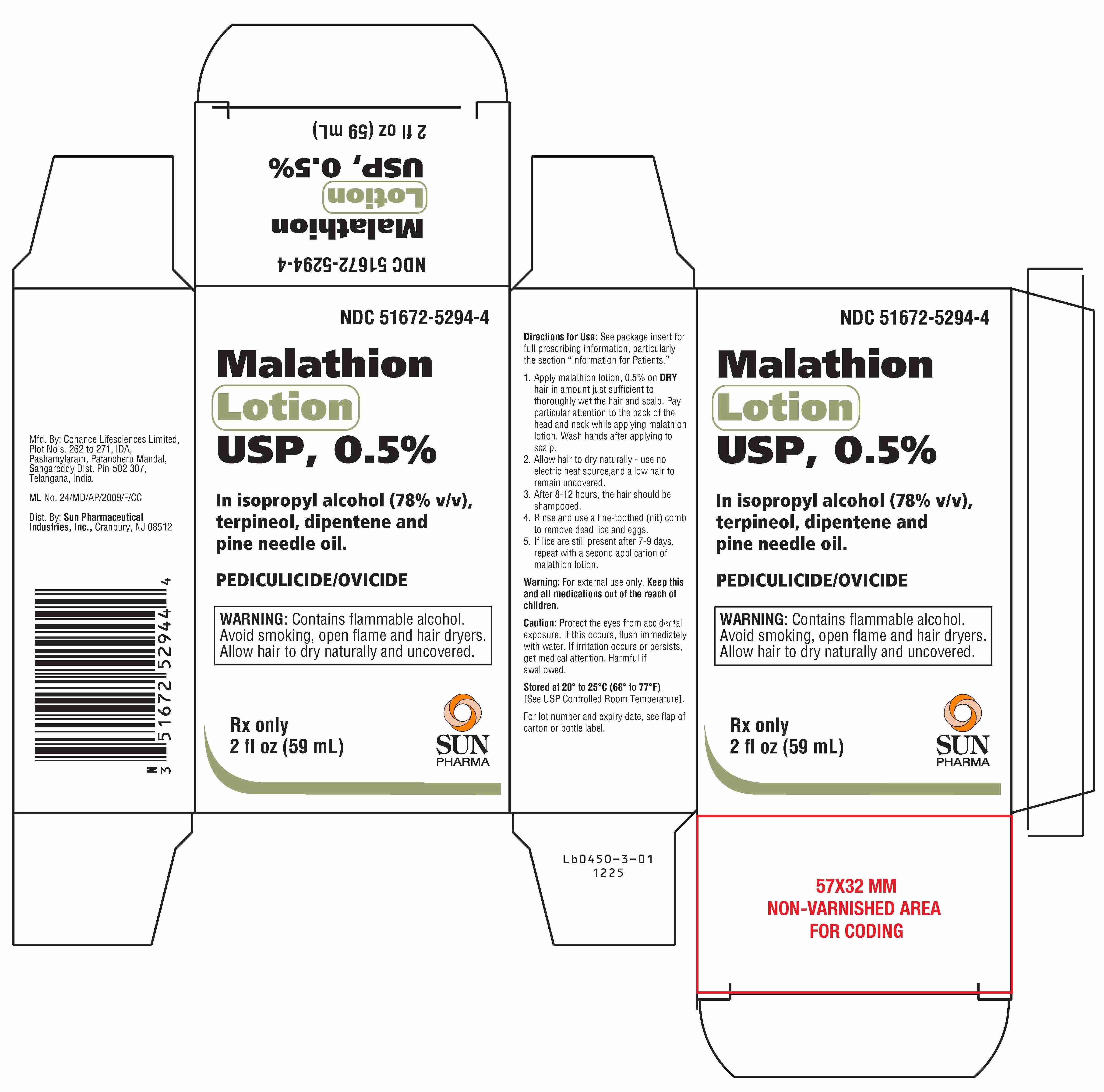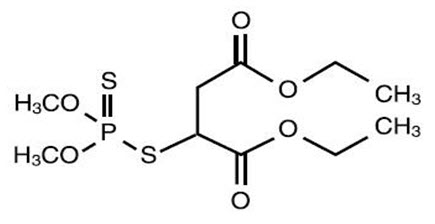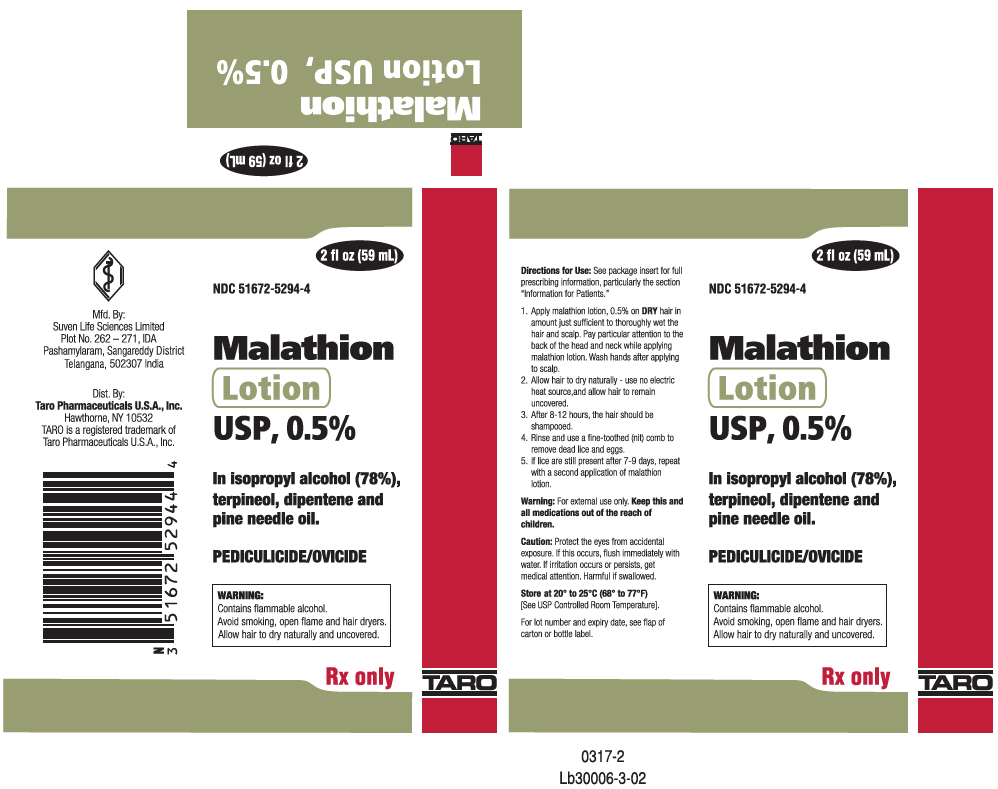 DRUG LABEL: Malathion
NDC: 51672-5294 | Form: LOTION
Manufacturer: Sun Pharmaceutical Industries, Inc.
Category: prescription | Type: HUMAN PRESCRIPTION DRUG LABEL
Date: 20260114

ACTIVE INGREDIENTS: MALATHION 0.0005 g/1 mL
INACTIVE INGREDIENTS: ISOPROPYL ALCOHOL; TERPINEOL; LIMONENE, (+/-)-; PINE NEEDLE OIL (PINUS SYLVESTRIS)

Malathion Lotion USP,0.5%

Rx Only

For topical use only. Not for oral or ophthalmic use.

DESCRIPTION

Malathion lotion contains 0.005 g of malathion per mL in a vehicle of isopropyl alcohol (78% v/v), terpineol, dipentene, and pine needle oil. The chemical name of malathion is (±) - [(dimethoxyphosphinothioyl) - thio] butanedioic acid diethyl ester. Malathion has a molecular weight of 330.36, represented by C10H19O6PS2, and has the following chemical structure:

CLINICAL PHARMACOLOGY

Malathion is an organophosphate agent which acts as a pediculicide by inhibiting cholinesterase activity in vivo.Inadvertent transdermal absorption of malathion has occurred from its agricultural use. In such cases, acute toxicity was manifested by excessive cholinergic activity, i.e., increased sweating, salivary and gastric secretion, gastrointestinal and uterine motility, and bradycardia (see OVERDOSAGE).

Because the potential for transdermal absorption of malathion from malathion lotion is not known at this time, strict adherence to the dosing instructions regarding its use in children, method of application, duration of exposure, and frequency of application is required.

INDICATIONS AND USAGE

Malathion lotion is indicated for patients infected with Pediculus humanus capitis(head lice and their ova) of the scalp hair.

CONTRAINDICATIONS

Malathion lotion is contraindicated for neonates and infants because their scalps are more permeable and may have increased absorption of malathion. Malathion lotion should also not be used on individuals known to be sensitive to malathion or any of the ingredients in the vehicle.

WARNINGS

1. Malathion lotion is flammable.The lotion and wet hair should not be exposed to open flames or electric heat sources, including hair dryers and electric curlers. Do not smoke while applying lotion or while hair is wet.
  Allow hair to dry naturally and to remain uncovered after application of malathion lotion.
2. Malathion lotion should only be used on children under the direct supervision of an adult.
3. If malathion lotion comes into contact with the eyes, flush immediately with water. Consult a physician if eye irritation persists.
4. If skin irritation occurs, discontinue use of product until irritation clears. Reapply the malathion lotion, and if irritation reoccurs, consult a physician.
5. Chemical burns including second-degree burns and stinging sensations may occur with the use of malathion lotion.

General

Keep out of reach of children. Close eyes tightly during product application. If accidentally placed in the eye, flush immediately with water. Use only on scalp hair.

Information to Patients

1. Malathion lotion is flammable.The lotion and hair wet with lotion should not be exposed to open flames or electric heat sources, including hair dryers and electric curlers. Do not smoke while applying lotion or while hair is wet.
  The person applying malathion lotion should wash hands after application. Allow hair to dry naturally and to remain uncovered after application of malathion lotion.
2. Malathion lotion should only be used on children under the direct supervision of an adult. Children should be warned to stay away from lighted cigarettes, open flames, and electric heat sources while the hair is wet.
3. In case of accidental ingestion of malathion lotion by mouth, seek medical attention immediately.
4. If you are pregnant or nursing, you should contact your physician before using malathion lotion.
5. If malathion lotion comes into contact with the eyes, flush immediately with water. Consult a physician if eye irritation persists or if visual changes occur.
6. If skin irritation occurs, wash scalp and hair immediately. If the irritation clears, malathion lotion may be reapplied. If irritation reoccurs, consult a physician.
7. Burns and stinging sensations may occur when using malathion lotion.
8. Apply malathion lotion on the scalp hair in an amount just sufficient to thoroughly wet hair and scalp. Pay particular attention to the back of the head and neck when applying malathion lotion. Anyone applying malathion lotion should wash hands immediately after the application process is complete.
9. Allow hair to dry naturally and to remain uncovered. Shampoo hair after 8 to 12 hours, again paying attention to the back of the head and neck while shampooing.
10. Rinse hair and use a fine - toothed (nit) comb to remove dead lice and eggs.
11. If lice are still present after 7 - 9 days, repeat with a second application of malathion lotion.
12. Further treatment is generally not necessary. Other family members should be evaluated by a physician to determine if infested, and if so, receive treatment.

Laboratory Tests

There are no special laboratory tests needed in order to use this medication.

Carcinogenesis, mutagenesis and impairment of fertility have not been studied with malathion lotion (0.5% pharmaceutical grade malathion). However, following long-term oral administration of technical grade malathion to rodents via dietary supplementation, increased incidences of hepatocellular neoplastic lesions were observed in B6C3F1 mice dosed for 18 months at malathion doses greater than 1500 mg/kg/day, and in female F344 rats dosed for 2 years at malathion doses greater than 400 mg/kg/day. These tumors occurred only in association with severe hepatic toxicity and chronic suppression of acetylcholinesterase activity, or at doses causing excessive mortality. Based on body surface area, doses at which carcinogenic effects were observed in rodents following life-time exposures to malathion were approximately 14- to 26-fold greater than the maximum dose anticipated in a 10 kg child following a single use of malathion lotion, assuming 100% bioavailability. Actual systemic exposures are expected to be less than 10% of the administered dose.

The malathion of greater than pharmaceutical-grade purity used in malathion lotion has not been tested for genotoxicity. The technical-grade malathion (95% pure) was found to be negative in Salmonella typhimurium, equivocally positive in the mouse lymphoma cell assay, and positive in in vitrochromosomal aberration and sister chromatid exchange assays. Fifteen separate in vitrogene mutation studies with malathion of unknown purity have reported negative results, while three studies reported malathion to be mutagenic in bacterial cells. Both technical grade (94–96.5%) and purified (98-99%) malathion have been reported to cause chromosomal aberrations and sister chromatid exchanges in vitroin human and hamster cell lines. In vivochromosomal aberration and micronucleus studies of technical- grade malathion are reported to be positive, whereas an in vivochromosomal aberration study of >99% pure malathion was reported to be negative. Furthermore, mice exposed to malathion in their drinking water for 7 weeks demonstrated no evidence of chromosome damage in bone marrow cells, spermatogonia, or primary spermatocytes. Lack of details makes independent evaluation of the results of these assays impossible. Ashby and Purchase have suggested that impurities may be responsible for some of the observed genetic activity of malathion.

Reproduction studies performed with malathion in rats at doses over 180 fold greater than those anticipated in a 60 kg adult (based on body surface area and assuming 100% bioavailability) revealed no evidence of impaired fertility.

Pregnancy

Pregnancy Category B

There was no evidence of teratogenicity in studies in rats and rabbits at doses up to 900 mg/kg/day and 100 mg/kg/day malathion, respectively. A study in rats failed to show any gross fetal abnormalities attributable to feeding malathion up to 2,500 ppm (~ 200 mg/kg/day) in the diet during a three - generation evaluation period. These doses were approximately 40 to 180 times higher than the dose anticipated in a 60 kg adult (based on body surface area and assuming 100% bioavailability). Because animal reproduction studies are not always predictive of human responses, this drug should be used (or handled) during pregnancy only if clearly needed.

Nursing Mothers

Malathion in an acetone vehicle has been reported to be absorbed through human skin to the extent of 8% of the applied dose. However, percutaneous absorption from the malathion lotion, 0.5% formulation has not been studied, and it is not known whether malathion is excreted in human milk. Because many drugs are excreted in human milk, caution should be exercised when malathion lotion is administered to (or handled by) a nursing mother.

Pediatric Use

The safety and effectiveness of malathion lotion in children less than 6 years of age has not been established via well-controlled trials.

ADVERSE REACTIONS

Malathion has been shown to be irritating to the skin and scalp. Other adverse reactions reported are chemical burns including second-degree burns. Accidental contact with the eyes can result in mild conjunctivitis.

It is not known if malathion lotion has the potential to cause contact allergic sensitization.

OVERDOSAGE

Consideration should be given, as part of the treatment program, to the high concentration of isopropyl alcohol in the vehicle.

Malathion, although a weaker cholinesterase inhibitor than some other organophosphates, may be expected to exhibit the same symptoms of cholinesterase depletion after accidental ingestion orally. If accidentally swallowed, vomiting should be induced promptly or the stomach lavaged with 5% sodium bicarbonate solution.

Severe respiratory distress is the major and most serious symptom of organophosphate poisoning requiring artificial respiration, and atropine may be needed to counteract the symptoms of cholinesterase depletion.

Repeat analyses of serum and RBC cholinesterase may assist in establishing the diagnosis and formulating a long - range prognosis.

DOSAGE AND ADMINISTRATION

1. Apply malathion lotion on DRYhair in amount just sufficient to thoroughly wet the hair and scalp. Pay particular attention to the back of the head and neck while applying malathion lotion. Wash hands after applying to scalp.
2. Allow hair to dry naturally - use no electric heat source, and allow hair to remain uncovered.
3. After 8 to 12 hours, the hair should be shampooed.
4. Rinse and use a fine - toothed (nit) comb to remove dead lice and eggs.
5. If lice are still present after 7 - 9 days, repeat with a second application of malathion lotion.

Further treatment is generally not necessary. Other family members should be evaluated by a physician to determine if infested, and if so, receive treatment.

Clinical Studies

Two controlled clinical trials evaluated the pediculicidal activity of malathion lotion. Patients applied the lotion to the hair and scalp in quantities, up to a maximum of 2 fl. oz., sufficient to thoroughly wet the hair and scalp. The lotion was allowed to air dry and was shampooed with Prell shampoo 8 to 12 hours after application. Patients in both the malathion lotion group and in the vehicle group were examined immediately after shampooing, 24 hours after, and 7 days after for the presence of live lice. Results are shown in the following table:

Number of Patients Without Live Scalp Lice
Treatment | Immediately After | 24 Hrs . After | 7 Days After
Malathion lotion | 129/129 | 122/129 | 114/126
Malathion vehicle | 105/105 | 63/105 | 31/105

The presence or absence of ova at day 7 was not evaluated in these studies. The presence or absence of live lice or ova at 14 days following treatment was not evaluated in these studies. The residual amount of malathion on hair and scalp is unknown.

HOW SUPPLIED

Malathion Lotion USP, 0.5%, is supplied in bottles of 2 fl. oz. (59 mL) NDC 51672-5294-4.

STORAGE AND HANDLING

Store at 20°to 25°C (68°to 77°F)[see USP Controlled Room Temperature].

Flammable. Keep away from heat and open flame.

Mfd by: Cohance Lifesciences Limited, Plot No’s. 262 to 271, IDA, Pashamylaram, Patancheru Mandal, Sangareddy Dist. Pin-502 307,

Telangana, India.

ML No. 24/MD/AP/2009/F/CC
Dist. by: Sun Pharmaceutical Industries, Inc., Cranbury, NJ 08512
Issued: December 2025

Lb0450-4-01 1225

PRINCIPAL DISPLAY PANEL - 59 mL Bottle Carton

2 fl oz (59 mL)

NDC 51672-5294-4

Malathion
(Lotion)
USP, 0.5%

In isopropyl alcohol (78%),
terpineol, dipentene and
pine needle oil.

PEDICULICIDE/OVICIDE

WARNING:
Contains flammable alcohol.
Avoid smoking, open flame and hair dryers.
Allow hair to dry naturally and uncovered.

Rx only